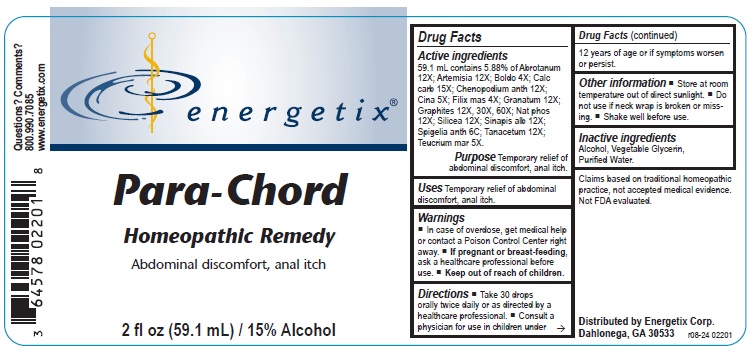 DRUG LABEL: Para-Chord
NDC: 64578-0073 | Form: LIQUID
Manufacturer: Energetix Corporation
Category: homeopathic | Type: HUMAN OTC DRUG LABEL
Date: 20250715

ACTIVE INGREDIENTS: ARTEMISIA ABROTANUM FLOWERING TOP 12 [hp_X]/59.1 mL; ARTEMISIA VULGARIS ROOT 12 [hp_X]/59.1 mL; PEUMUS BOLDUS LEAF 4 [hp_X]/59.1 mL; OYSTER SHELL CALCIUM CARBONATE, CRUDE 15 [hp_X]/59.1 mL; DYSPHANIA AMBROSIOIDES 12 [hp_X]/59.1 mL; ARTEMISIA CINA PRE-FLOWERING TOP 5 [hp_X]/59.1 mL; DRYOPTERIS FILIX-MAS ROOT 4 [hp_X]/59.1 mL; PUNICA GRANATUM ROOT BARK 12 [hp_X]/59.1 mL; GRAPHITE 12 [hp_X]/59.1 mL; SODIUM PHOSPHATE, DIBASIC 12 [hp_X]/59.1 mL; SILICON DIOXIDE 12 [hp_X]/59.1 mL; WHITE MUSTARD SEED 12 [hp_X]/59.1 mL; SPIGELIA ANTHELMIA 6 [hp_C]/59.1 mL; TANACETUM VULGARE TOP 12 [hp_X]/59.1 mL; TEUCRIUM MARUM 5 [hp_X]/59.1 mL
INACTIVE INGREDIENTS: WATER; GLYCERIN; ALCOHOL

Para-Chord

ACTIVE INGREDIENT

Active ingredients59.1 mL contains 5.88% of: Abrotanum 12X; Artemisia 12X; Boldo 4X; Calcarea carb 15X; Chenopodium anth 12X; Cina 5X; Filix mas 4X; Granatum 12X; Graphites 12X, 30X, 60X; Nat phos 12X; Silicea 12X; Sinapis alb 12X; Spigelia anth 6C; Tanacetum 12X; Teucrium mar 5X

Claims based on traditional homeopathic practice, not accepted medical evidence.

Not FDA evaluated.

Uses

Temporary relief of abdominal discomfort, anal itch.

Warnings

- In case of overdose, get medical help or contact a Poison Control Center right away.
- If pregnant or breast-feeding, ask a healthcare professional before use.

Keep out of reach of children.

Directions

- Take 30 drops orally twice daily or as directed by a healthcare professional.
- Consult a physician for use in children under 12 years of age or if symptoms worsen or persist.

Other information

- Store at room temperature out of direct sunlight.
- Do not use if neck wrap is broken or missing.
- Shake well before use.

Inactive ingredients

Alcohol, Vegetable Glycerin, Purified Water.

QUESTIONS

Distributed by Energetix Corp.

Dahlonega, GA 30533

Questions? Comments?

800.990.7085

www.energetix.com

PACKAGE LABEL

energetix

Para - Chord

Homeopathic Remedy

Abdominal discomfort, anal itch

2 fl oz (59.1 mL) / 15% Alcohol

PURPOSE

Temporary relief of abdominal discomfort, anal itch.